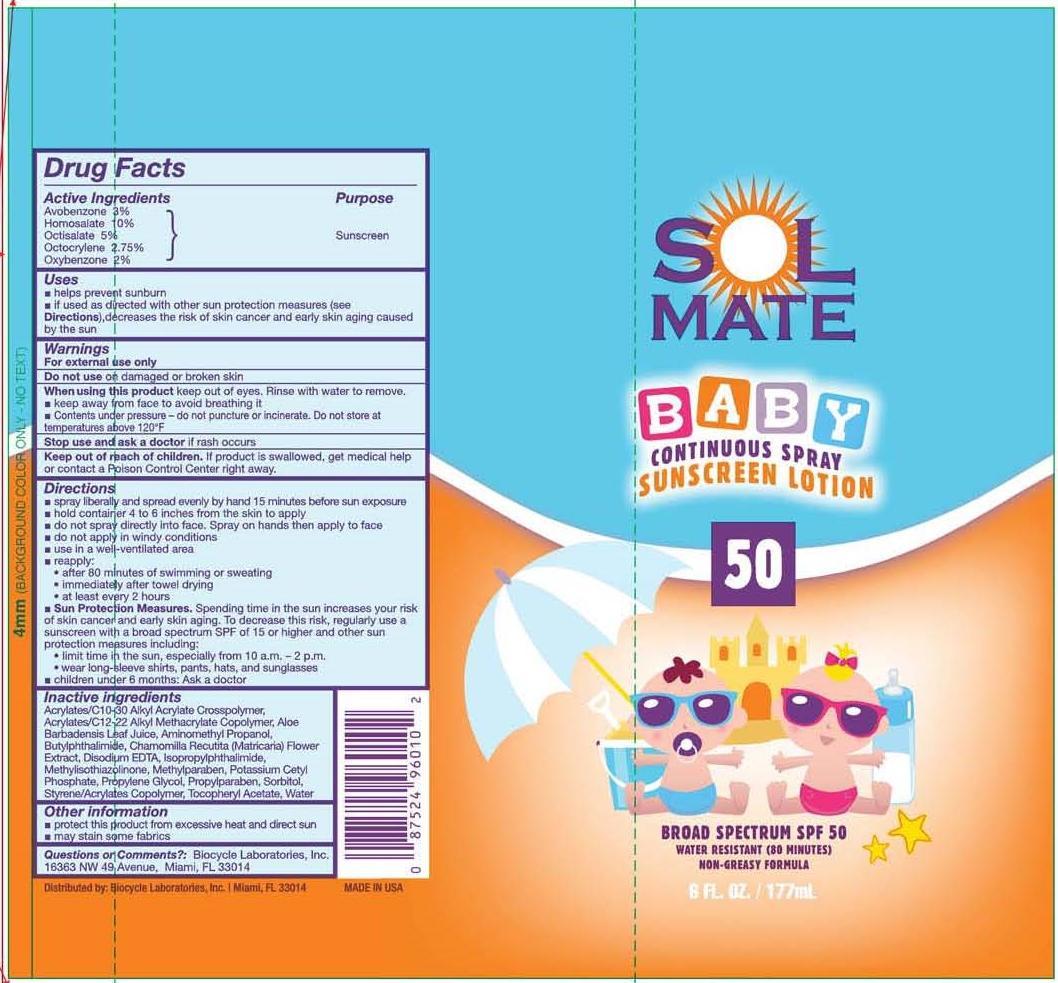 DRUG LABEL: SolMate
NDC: 13630-0060 | Form: SPRAY
Manufacturer: Prime Packaging, Inc.
Category: otc | Type: HUMAN OTC DRUG LABEL
Date: 20200117

ACTIVE INGREDIENTS: AVOBENZONE 30.1 mg/1 mL; HOMOSALATE 100.2 mg/1 mL; OCTISALATE 50.1 mg/1 mL; OCTOCRYLENE 27.6 mg/1 mL; OXYBENZONE 20 mg/1 mL
INACTIVE INGREDIENTS: CARBOMER COPOLYMER TYPE A; BUTYL ACRYLATE/C16-C20 ALKYL METHACRYLATE/METHACRYLIC ACID/METHYL METHACRYLATE COPOLYMER; ALOE VERA LEAF; AMINOMETHYLPROPANOL; 3-BUTYLPHTHALIDE; ISOPROPYLPHTHALIMIDE; EDETATE DISODIUM; METHYLPARABEN; POTASSIUM CETYL PHOSPHATE; PROPYLENE GLYCOL; CHAMOMILE; WATER; PROPYLPARABEN; SORBITOL; BUTYL METHACRYLATE/METHYL METHACRYLATE/METHACRYLIC ACID/STYRENE CROSSPOLYMER; .ALPHA.-TOCOPHEROL ACETATE; METHYLISOTHIAZOLINONE

Active ingredients

Avobenzone 3 %, Homosalate 10 %, Octisalate 5 %, Octocrylene 2.75 %, and Oxybenzone 2 %

Purpose

Sunscreen

Uses

- helps prevent sunburn
- if used as directed with other sun protection measures (see Directions), decreases the risk of skin cancer and early skin aging caused by the sun

Warnings

OTHER SAFETY INFORMATION

For external use only

Do not use on damaged or broken skin.

When using this product keep out of eyes. Rinse with water to remove.

- keep away from face to avoid breathing it.
- Contents under pressure - do not puncture or incinerate. Do not store at temperatures above 120^0F

Stop use and ask a doctor if rash occurs.

Keep out of reach of children. If product is swallowed, get medical help or contact a Poison Control Center right away.

Directions

- spray liberally and spread evenly by hand 15 minutes before sun exposure
- hold container 4 to 6 inches from the skin to apply
- do not spray directly into face. Spray on hands then apply to face
- do not apply in windy conditions
- use in well-ventilated areas.
- reapply:
  - after 80 minutes of swimming or sweating
  - immediately after towel drying
  - at least every 2 hours
- Sun Protection Measures. Spending time in the sun increases your risk of skin cancer and early skin aging. To decrease this risk, regularly use a sunscreen with broad spectrum SPF of 15 or higher and other sun protection measures including:
  - limit time in the sun, especially from 10 a.m. – 2 p.m.
  - wear long-sleeve shirts, pants, hats, and sunglasses
- children under 6 months: Ask a doctor

Inactive Ingredients

Acrylates/C10-30 Alkyl Acrylate Crosspolymer, Acrylates/C12-22 Alkyl Methacrylate Copolymer, Aloe Barbadensis Leaf Juice, Aminomethyl Propanol, Butylphthalimide, Chamomilla Recutita (Matricaria) Flower Extract, Disodium EDTA, Isopropylphthalimide, Methylisothiazolinone, Methylparaben, Potassium Cetyl Phosphate, Propylene Glycol, Propylparaben, Sorbitol, Styrene/Acrylates Copolymer, Tocopheryl Acetate, Water

Other information

- protect this product from excesive heat and direct sun
- may stain some fabrics

Questions or Comments? Biocycle Laboratories, Inc.

16363 NW 49th Avenue, Miami, FL 33014

PRINCIPAL DISPLAY PANEL - 177 mL Can Label

SOL

MATE

BABY

CONTINUOUS SPRAY

SUNSCREEN LOTION

50

BROAD SPECTRUM SPF 50

WATER RESISTANT (80 MINUTES)

NON-GREASY FORMULA

6 FL. OZ. / 177 mL